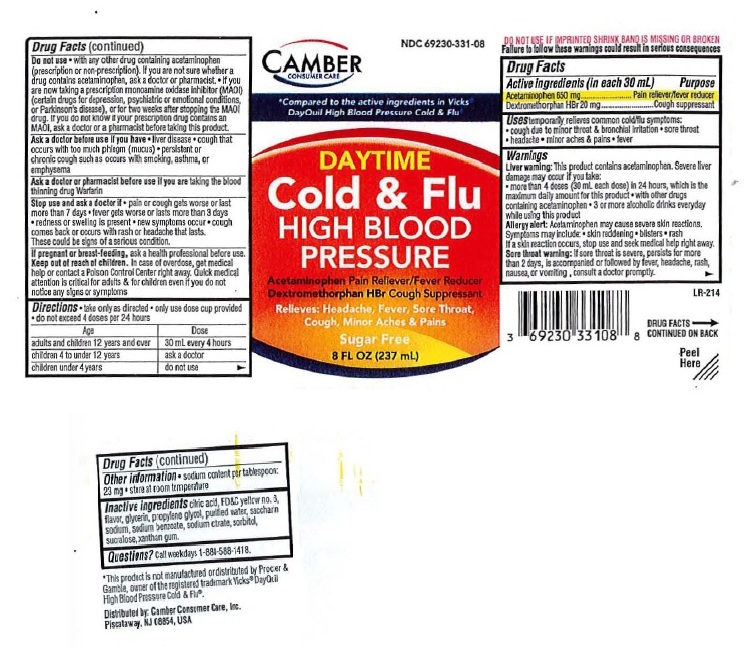 DRUG LABEL: Day time high blood pressure cold and flu
NDC: 69230-331 | Form: SOLUTION
Manufacturer: Camber Consumer Care
Category: otc | Type: HUMAN OTC DRUG LABEL
Date: 20250210

ACTIVE INGREDIENTS: ACETAMINOPHEN 650 mg/30 mL; DEXTROMETHORPHAN HYDROBROMIDE 20 mg/30 mL
INACTIVE INGREDIENTS: ANHYDROUS CITRIC ACID; FD&C YELLOW NO. 6; GLYCERIN; PROPYLENE GLYCOL; WATER; SODIUM SACCHARIN; SODIUM BENZOATE; ANHYDROUS TRISODIUM CITRATE; SORBITOL; SUCRALOSE; XANTHAN GUM

DAYTIME Cold & Flu High Blood Pressure

Drug Facts

Active ingredients
(in each 30 mL)

Acetaminophen 650 mg
Dextromethorphan HBr 20 mg

Purpose

Acetaminophen .................Pain reliever/Fever reducer
Dextromethorphan HBr ..........Cough suppressant

Uses
Temporarily relieves common cold/flu symptoms:

- cough due to minor throat & bronchial irritation
- sore throat
- headache
- minor aches & pains
- fever

Warnings

Liver warning: This product contains acetaminophen. Severe liver damage may occur if you take:

- more than 4 doses (30 mL each) of acetaminophen in 24 hours, which is the maximum daily amount for this product
- with other drugs containing acetaminophen
- 3 or more alcoholic drinks everyday while using this product

Allery alert: Acetaminophen may cause severe skin reactions. Symptoms may include:

- skin reddening
- blisters
- rash

If a skin reaction occurs, stop use and seek medical help right away

Sore throat warning: If sore throat is severe, persists for more than 2 days, is accompanied or followed by fever, headache, rash, nausea, or vomiting, consult a doctor promptly.

Do not use: • with any other drug containing acetaminophen (prescription or non-prescription). If you are not sure
whether a drug contains acetaminophen, ask a doctor or pharmacist. • if you are now taking a prescription monoamine
oxidase inhibitor (MAOI) (certain drugs for depression, psychiatric, or emotional conditions, or Parkinson's disease), or
for two weeks after stopping the MAOI drug. If you do not know if your prescription drug contains an MAOI, ask a doctor
or pharmacist before taking this product.

Ask a doctor before use if you have • liver disease •cough that occurs with too much phlegm (mucus) • persistent or
chronic cough such as occurs with smoking, asthma or emphysema

Ask a doctor or pharmacist before use if you are taking the blood thinning drug Warfarin

Stop use and ask a doctor if
• pain or cough gets worse or last more than 7 days • fever gets worse or lasts more than 3 days • redness or swelling
is present • new symptoms occur • cough comes back, or occurs with rash or headache that lasts. These could be signs
of a serious condition.

If pregnant or breast-feeding,

ask a health professional before use.

Keep out of reach of children.

Directions

- take only as directed
- only use dose cup provided
- do not take more than 4 doses per 24 hours

Age Dose
adults and children 12 years and over | 30 mL every 4 hours
children 4 to under 12 years | ask a doctor
children under 4 years | do not use

Other information

• sodium content per tablespoon: 23 mg
• store at room temperature

Inactive ingredients
citric acid, FD&C Yellow no. 6, flavor, glycerin, propylene glycol, purified water, saccharin sodium, sodium benzoate,
sodium citrate, sorbitol, sucralose, xanthan gum.

Questions? Call weekdays 1-888-588-1418

Package Label: DAYTIME Cold & Flu High Blood Pressure

------------------------

DAYTIME Cold & Flu High Blood Pressure

8 FL OZ (237 mL)

* This product is not manufactured or distributed by Proctor & Gamble, owner of the registered trademark Vicks®
DayQuil® High Blood Pressure Cold & Flu®.

Distributed by: Camber Consumer Care, Inc.
Piscataway, NJ 08854, USA

res